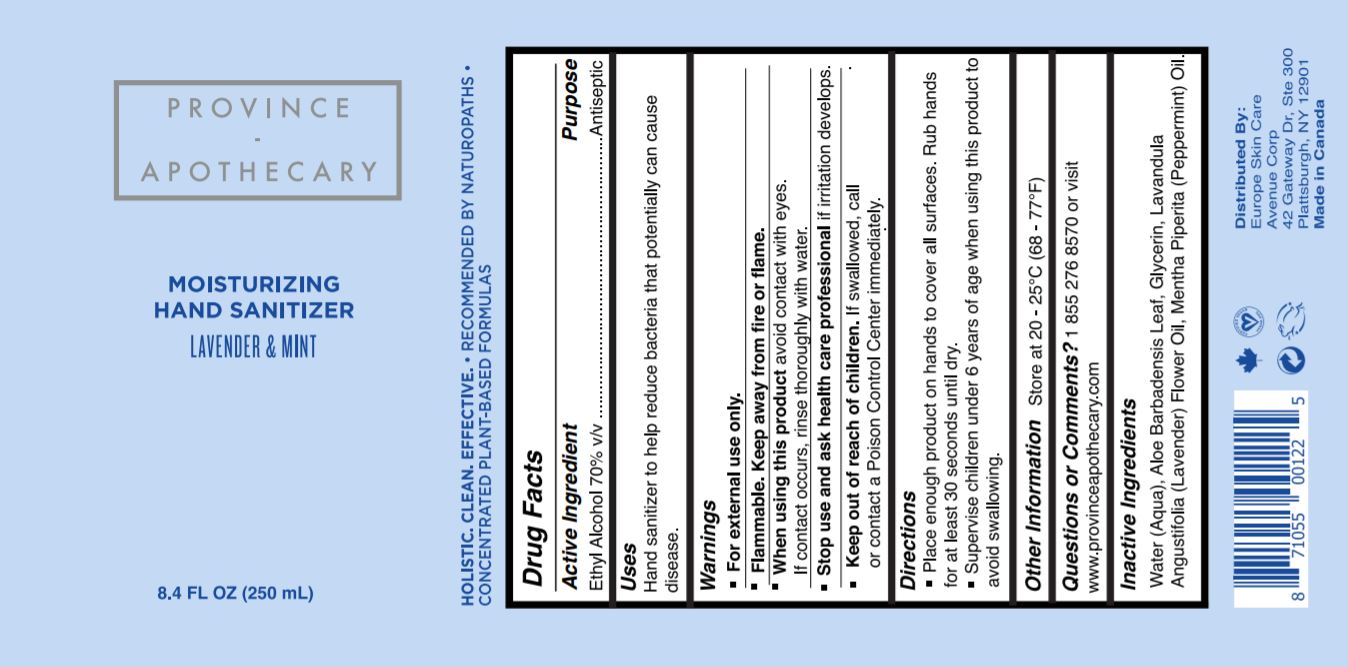 DRUG LABEL: MOISTURIZING HAND SANITIZER LAVENDER AND MINT
NDC: 72257-251 | Form: GEL
Manufacturer: PROVINCE APOTHECARY INC
Category: otc | Type: HUMAN OTC DRUG LABEL
Date: 20220101

ACTIVE INGREDIENTS: ALCOHOL 70 mL/100 mL
INACTIVE INGREDIENTS: LAVENDER OIL; PEPPERMINT OIL; ALOE VERA LEAF; GLYCERIN; WATER

MOISTURIZING GEL HAND SANITIZER LAVENDER & MINT 250 mL

ACTIVE INGREDIENT

Ethyl Alcohol 70%

PURPOSE

Antiseptic

USES

Hand sanitizer to help reduce bacteria that potentially can cause disease.

WARNINGS

For external use only. Flammable. Keep away from heat or flame

Do not use

■ in children less than 2 months of age

■ on open skin wounds

When using this product keep out of eyes, ears, and mouth. In case of contact with eyes, rinse eyes thoroughly with water.

Stop use and ask a doctor if irritation or rash occurs. These may be signs of a serious condition.

Keep out of reach of children. If swallowed, get medical help or contact a Poison Control Center right away.

When using this product

- Do not get into eyes.

Stop use and ask a doctor if

- condition worsens
  - symptoms persist for more than 7 days or clear up and occur again within a few days.

Keep out of reach of children.

- . If product is swallowed, get medical help or contact a Poison Control Center immediately.

DIRECTIONS

■ Place enough product on hands to cover all surfaces. Rub hands together until dry.

■ Supervise children under 6 years of age when using this product to avoid swallowing.

OTHER INFORMATION

■ Store between 15-30C (59-86F)

■ Avoid freezing and excessive heat above 40C (104F)

INACTIVE INGREDIENTS

Water (Aqua), Aloe Barbadensis Leaf Juice, Glycerin, Lavandula Angustifolia (Lavender) Flower Oil, Mentha Piperita (Peppermint) Oil.

QUESTIONS OR COMMENTS?

1 855 276 8570 or visit www.provinceapothecary.com